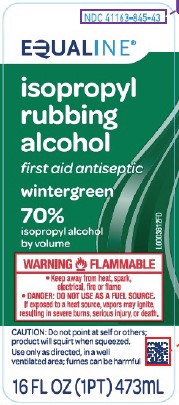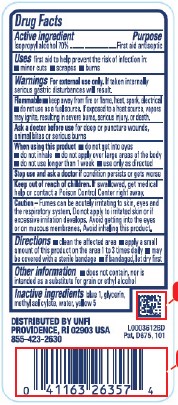 DRUG LABEL: Isopropyl Alcohol
NDC: 41163-845 | Form: LIQUID
Manufacturer: United Natural Foods, Inc. dba UNFI
Category: otc | Type: HUMAN OTC DRUG LABEL
Date: 20260226

ACTIVE INGREDIENTS: ISOPROPYL ALCOHOL 70 mL/100 mL
INACTIVE INGREDIENTS: GLYCERIN; METHYL SALICYLATE; WATER; FD&C YELLOW NO. 5; FD&C BLUE NO. 1

Equaline 845.003/845AE
70% IPA with Wintergreen

Active ingredient

Isopropyl alcohol 70%

Purpose

First aid antiseptic

Uses

helps prevent the risk of infection in:

- minor cuts
- scrapes
- burns

Warnings

For external use only. If taken internally serious gastric disturbances will result.

Flammable

- keep away from fire or flame, heat, spark, electrical.
- do not use as a fuel source. If exposed to a heat source, vapors may ignite, resulting in severe burns, serious injury, or death.

Ask a doctor before use

for deep or puncture wounds, animal bites or serious burns

When using this product

- do not get into eyes
- do not inhale
- do not apply over large areas of the body
- do not use longer than 1 week
- use only as directed

Stop use and ask a doctor if

condition persists or gets worse

Keep out of reach of children.

If swallowed, get medical help or contact a Poison Control Center right away.

Caution

Fumes can be acutely irritating to skin, eyes and the respiratory system. Do not apply to irritated skin or if excessive irritation develops. Avoid gettting into the eyes or on mucous membranes. Avoid inhaling this product.

Directions

- clean the affected area
- apply a small amount of this product on the area 1 to 3 times daily
- may be covered with a sterile bandage
- if bandaged, let dry first

Other information

- does not contain, nor is intended as a substitute for grain or ethyl alcohol

Inactive ingredients

blue 1, glycerin, methyl salicylate, water, yellow 5

ADVERSE REACTION

DISTRIBUTED BY UNFI

PROVIDENCE, RI 02903 USA

855-423-2630

Pat. D675, 101

Principal display panel

NDC 41163-845-43

EQUALINE®

isopropyl rubbing alcohol

first aid antiseptic

wintergreen

70% isopropyl alcohol by volume

WARNING FLAMMABLE

- Keep away from heat, spark, electrical, fire or flames
- DANGER: DO NOT USE AS A FUEL SOURCE.

If exposed to a heat source, vapors may ignite, resulting in severe burns, serious injury, or death.

CAUTION: Do not point at self or others; product will squirt when squeezed.

Use only as directed, in a well-ventilated area; fumes can be harmful.

16 FL OZ (1 PT) 473 mL